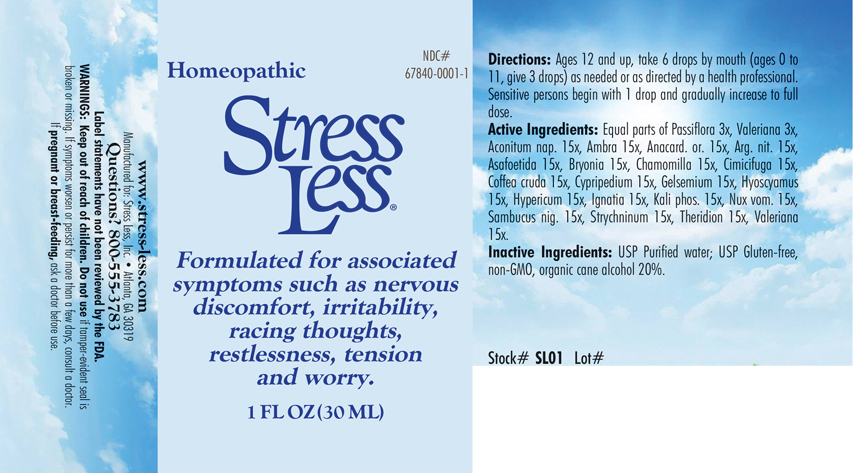 DRUG LABEL: Stress Less
NDC: 67840-0001 | Form: LIQUID
Manufacturer: Stress Less, Inc.
Category: homeopathic | Type: HUMAN OTC DRUG LABEL
Date: 20180110

ACTIVE INGREDIENTS: ACONITUM NAPELLUS 15 [hp_X]/1 mL; AMBERGRIS 15 [hp_X]/1 mL; SEMECARPUS ANACARDIUM JUICE 15 [hp_X]/1 mL; SILVER NITRATE 15 [hp_X]/1 mL; ASAFETIDA 15 [hp_X]/1 mL; BRYONIA ALBA ROOT 15 [hp_X]/1 mL; MATRICARIA RECUTITA 15 [hp_X]/1 mL; BLACK COHOSH 15 [hp_X]/1 mL; ARABICA COFFEE BEAN 15 [hp_X]/1 mL; CYPRIPEDIUM PARVIFOLUM ROOT 15 [hp_X]/1 mL; GELSEMIUM SEMPERVIRENS ROOT 15 [hp_X]/1 mL; HYOSCYAMUS NIGER 15 [hp_X]/1 mL; HYPERICUM PERFORATUM 15 [hp_X]/1 mL; STRYCHNOS IGNATII SEED 15 [hp_X]/1 mL; POTASSIUM PHOSPHATE, DIBASIC 15 [hp_X]/1 mL; STRYCHNOS NUX-VOMICA SEED 15 [hp_X]/1 mL; SAMBUCUS NIGRA FLOWERING TOP 15 [hp_X]/1 mL; STRYCHNINE 15 [hp_X]/1 mL; THERIDION CURASSAVICUM 15 [hp_X]/1 mL; VALERIAN 15 [hp_X]/1 mL; PASSIFLORA INCARNATA FLOWERING TOP 3 [hp_X]/1 mL
INACTIVE INGREDIENTS: ALCOHOL

Stress Less

QUESTIONS SECTION

Manuractured for Stress Less, Inc., Atlanta, GA 30319

Questions? 800-555-3783

INDICATIONS & USAGE SECTION

Stress Less: Formulated for associated symptoms such as nervous discomfort, irritability, racing thoughts, restlessness, tension and worry.

DOSAGE & ADMINISTRATION SECTION

Directions: Ages 12 and up, take 6 drops by mouth (ages 0 to 11, give 3 drops) as needed or as directed by a health professional. Sensitive persons begin with 1 drop and gradually increase to full dose.

OTC - ACTIVE INGREDIENT SECTION

Equal parts of Passiflora 3x, Valeriana 3x Aconitum nap. 15x, Ambra 15x, Anacard. or. 15x, Arg. nit. 15x, Asafoetida 15x, Bryonia 15x, Chamomilla 15x, Cimicifuga 15x, Coffea cruda 15x, Cypripedium 15x, Gelsemium 15x, Hyoscyamus 15x, Hypericum 15x, Ignatia 15x, Kali phos. 15x, Nux vom. 15x, Sambucus nig. 15x, Strychninum 15x, Theridion 15x, Valeriana 15x, .

OTC - PURPOSE SECTION

Formulated for associated symptoms such as nervous discomfort, irritability, racing thoughts, restlessness, tension and worry.

INACTIVE INGREDIENT SECTION

Inactive Ingredients: USP Purified Water; USP Gluten-free, non-GMO, organic cane alcohol 20%.

WARNINGS SECTION

Warning: Keep ou of reach of children. Do not use if tamper-evident seal is broken or missing. If symptoms worsen or persist for more than a few days, consult a doctor. If pregnant or breast-feeding, ask a doctor before use.

OTC - PREGNANCY OR BREAST FEEDING SECTION

If pregnant or breast-feeding, ask a doctor before use.

OTC - KEEP OUT OF REACH OF CHILDREN SECTION

Keep out of reach of children.